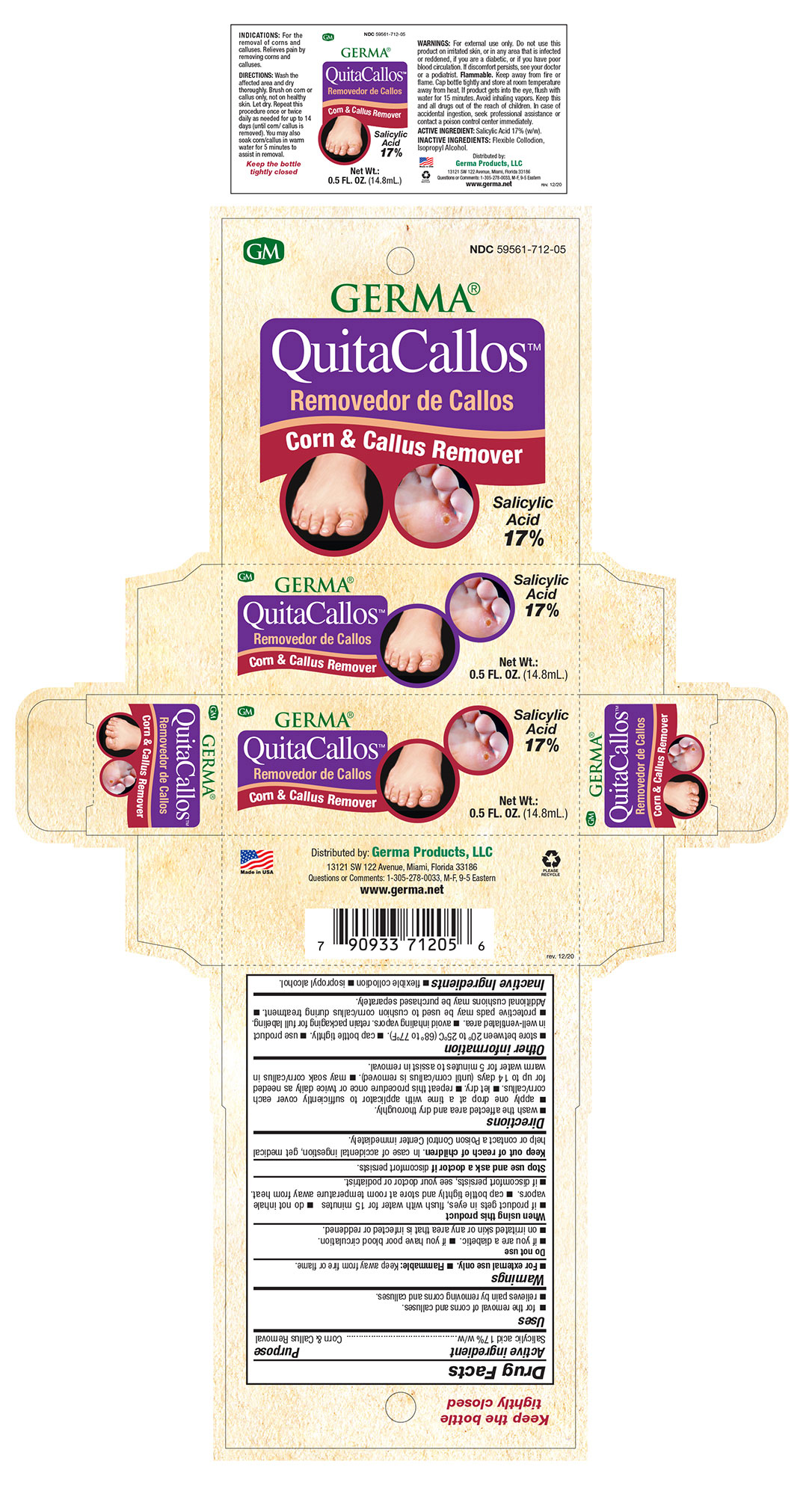 DRUG LABEL: Quita Callos Corn and Callus Remover
NDC: 73635-5811 | Form: LIQUID
Manufacturer: Germa Products, LLC
Category: otc | Type: HUMAN OTC DRUG LABEL
Date: 20251010

ACTIVE INGREDIENTS: SALICYLIC ACID 170 mg/1 mL
INACTIVE INGREDIENTS: ALCOHOL; ISOPROPYL ALCOHOL; CAMPHOR (SYNTHETIC); CASTOR OIL

Quita Callos Analgesic Liquid

Active Ingredient

Salicylic Acid 17%

Uses

for the removal of common warts. The common wart is easily recognized by the rough “cauliflower-like” appearance of the surface.

INDICATIONS AND USAGE

for the removal of common warts. The common wart is easily recognized by the rough “cauliflower-like” appearance of the surface.

Purpose

Wart Remover Liquid

Warnings

For external use only. Flammable: Keep away from fire or flame.
Do not use: in or near eyes or mucous membranes. On irritated skin. If prone to allergic reaction to any ingredient in this product. On moles, birthmarks, warts with hair growing from them, genital warts, or warts on the face or mucous membranes. On any area that is infected or reddened. If you are a diabetic, or have poor blood circulation n on large area of the body, on wounds or damaged skin.
When using this product: If product gets in eyes, flush with water for 15 minutes. Do not inhale vapors. Cap bottle tightly and store at room temperature away from heat.
If discomfort persists, see your doctor.
Stop use and ask a doctor if; Irritation occurs n condition worsens or does not improve or discomfort persists. If pregnant or breast-feeding. Ask a health professional before use. Keep out of reach of children. In case of accidental ingestion, get medical help or contact a Poison Control Center immediately.

Warnings

• Keep out of reach of children. In case of accidental ingestion, get medical help or contact a Poison Control Center immediately.

Other Information

Store between 20º to 25ºC (68º to 77ºF). Cap bottle tightly. Use product in well ventilated area. Avoid inhaling vapors. Retain packaging for full labeling.

Directions

• Wash affected area and dry thoroughly.

• Apply one drop at a time with applicator to sufficiently cover each wart.

• Let dry.

• Repeat this procedure once or twice daily as needed for up to 2 weeks.

Inactive Ingredients

Flexible Collodion (Alcohol, Camphor, Mineral Oil), and Isopropyl Alcohol.

PACKAGE LABEL

Quita Callos